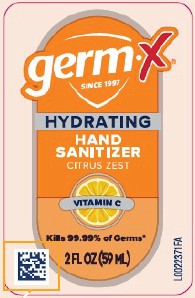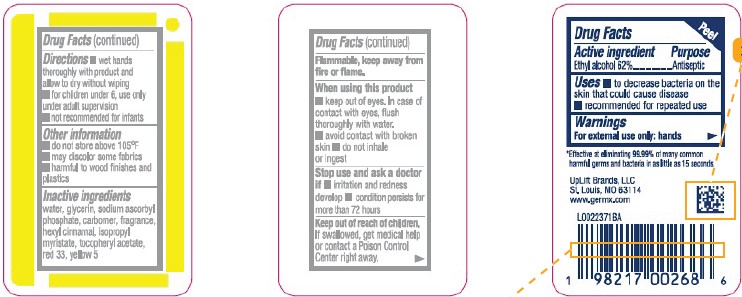 DRUG LABEL: ETHYL ALCOHOL
NDC: 83986-973 | Form: LIQUID
Manufacturer: UpLift Brands, LLC
Category: otc | Type: HUMAN OTC DRUG LABEL
Date: 20251103

ACTIVE INGREDIENTS: ALCOHOL 62 mL/100 mL
INACTIVE INGREDIENTS: .ALPHA.-TOCOPHEROL ACETATE; FD&C YELLOW NO. 5; CARBOMER HOMOPOLYMER, UNSPECIFIED TYPE; ISOPROPYL MYRISTATE; .ALPHA.-HEXYLCINNAMALDEHYDE; D&C RED NO. 33; WATER; GLYCERIN; SODIUM ASCORBYL PHOSPHATE

Germ-X D73.000/D73AB
Germ-X Hydrating Hand Sanitizer + Vitamin C

Active ingredient

Ethyl alcohol 62%

Purpose

Antiseptic

Uses

- to decrease bacteria on the skin that could cause disease
- recommended for repeated use

Warnings

For external use only: hands

Flammable, keep away from fire or flame.

When using this product

- keep out of eyes. In case of contact with eyes, flush thoroughly with water.
- avoid contact with broken skin
- do not inhale or ingest

Stop use and ask a doctor if

- irritation and redness develop
- condition persists for more than 72 hours

Keep out of reach of children.

If swallowed, get medical help or contact a Poison Control Center right away.

Directions

- wet hands thoroughly with product and allow to dry without wiping
- for children under 6, use only under adult supervision
- not recommended for infants

Other information

- do not store above 105⁰ F
- may discolor some fabrics
- harmful to wood finishes and plastics

Inactive ingredients

water, glycerin, sodium ascorbyl phosphate, carbomer, fragrance, hexyl cinnamal, isopropyl myristate, tocopheryl acetate, red 33, yellow 5

Claims

*Effective at eliminating 99.99% of many common harmful germs and bacteria in as little as 15 seconds.

Adverse Reaction

UpLift Brands, LLC

St. Louis, MO 63114

www.germx.com

Principal Display Panel

germ X®

SINCE 1997

HYDRATING

HAND SANITIZER

CITRUS ZEST

VITAMIN C

Kills 99.99% of Germs*

2 FL OZ (59 mL)